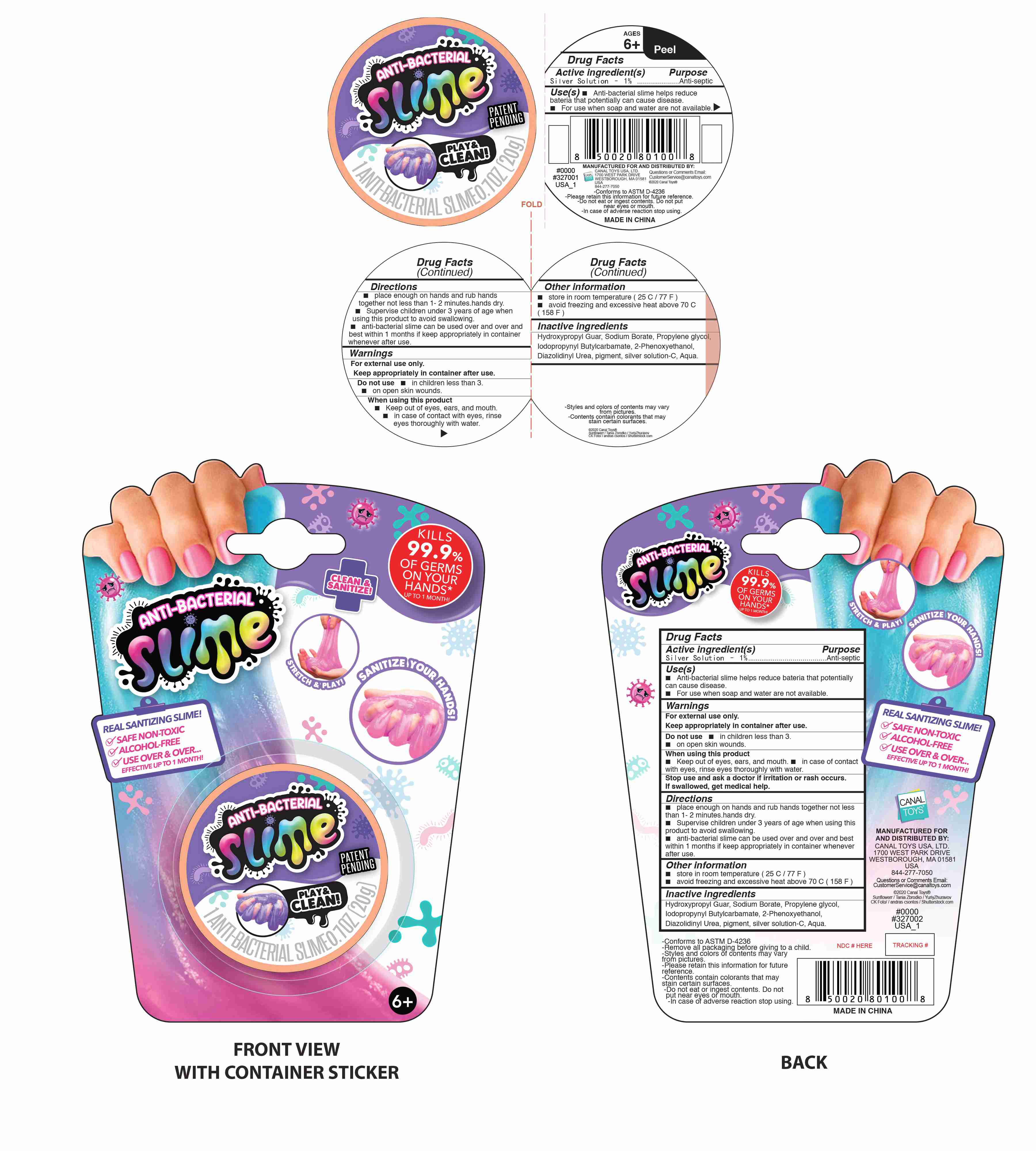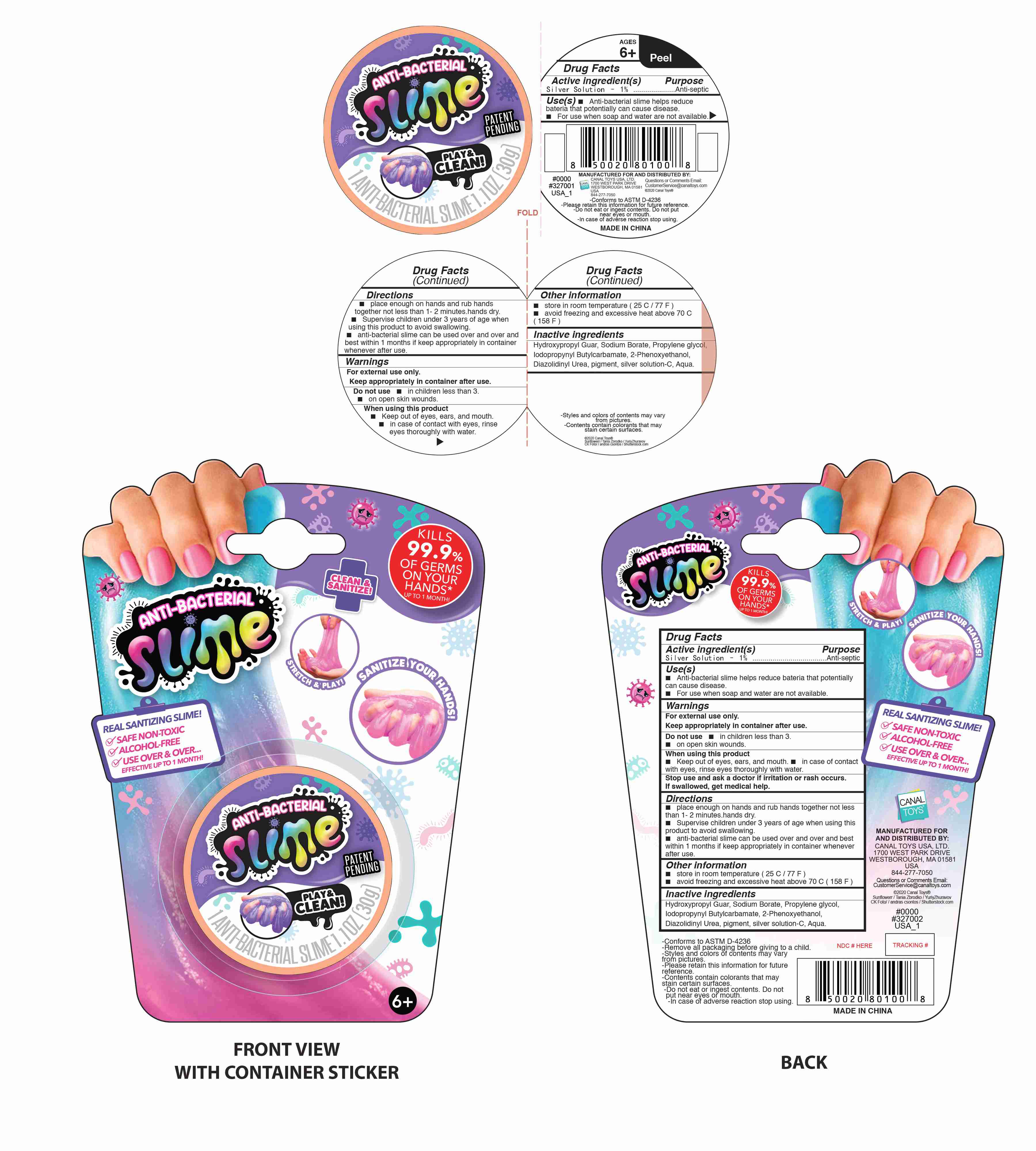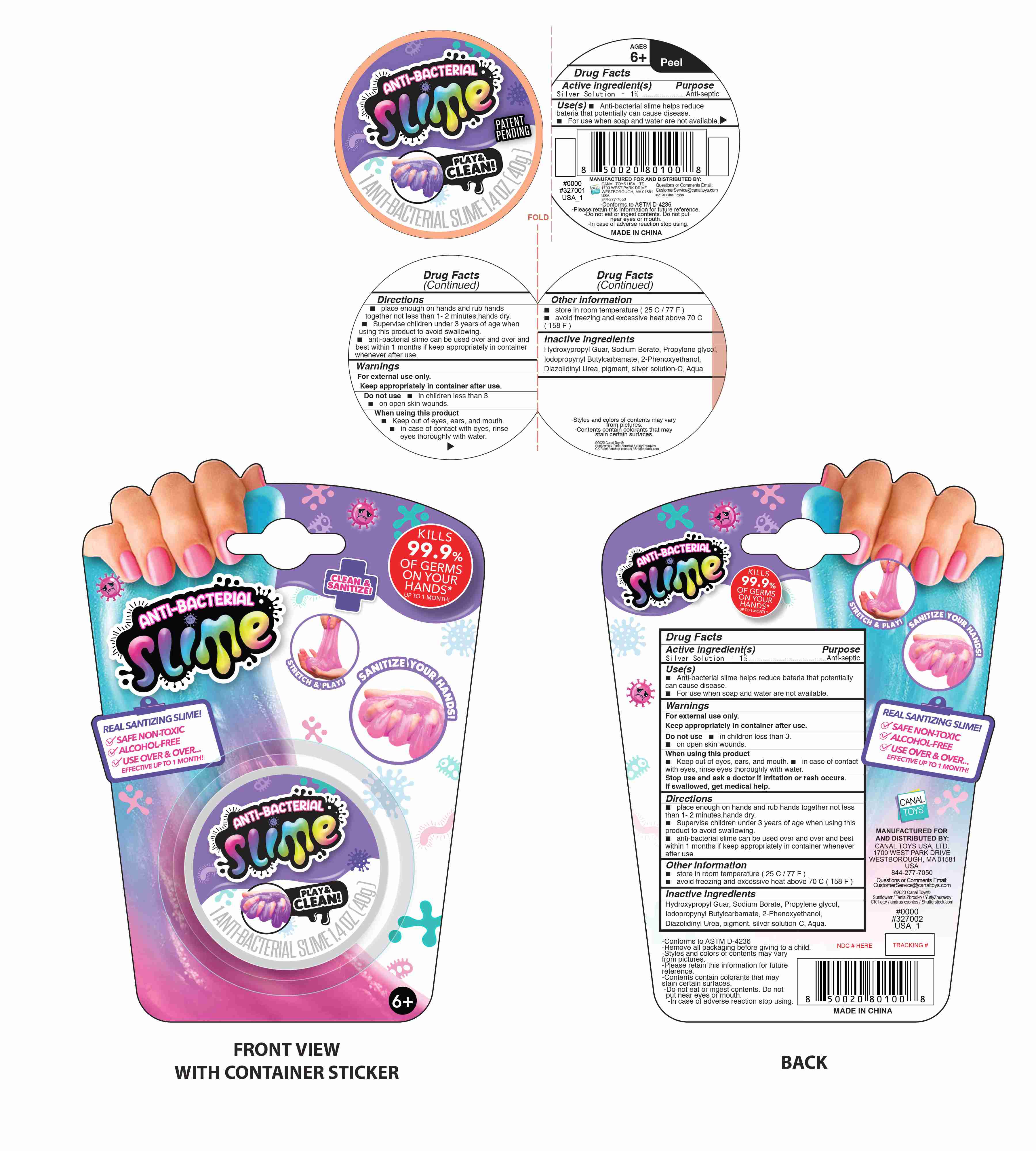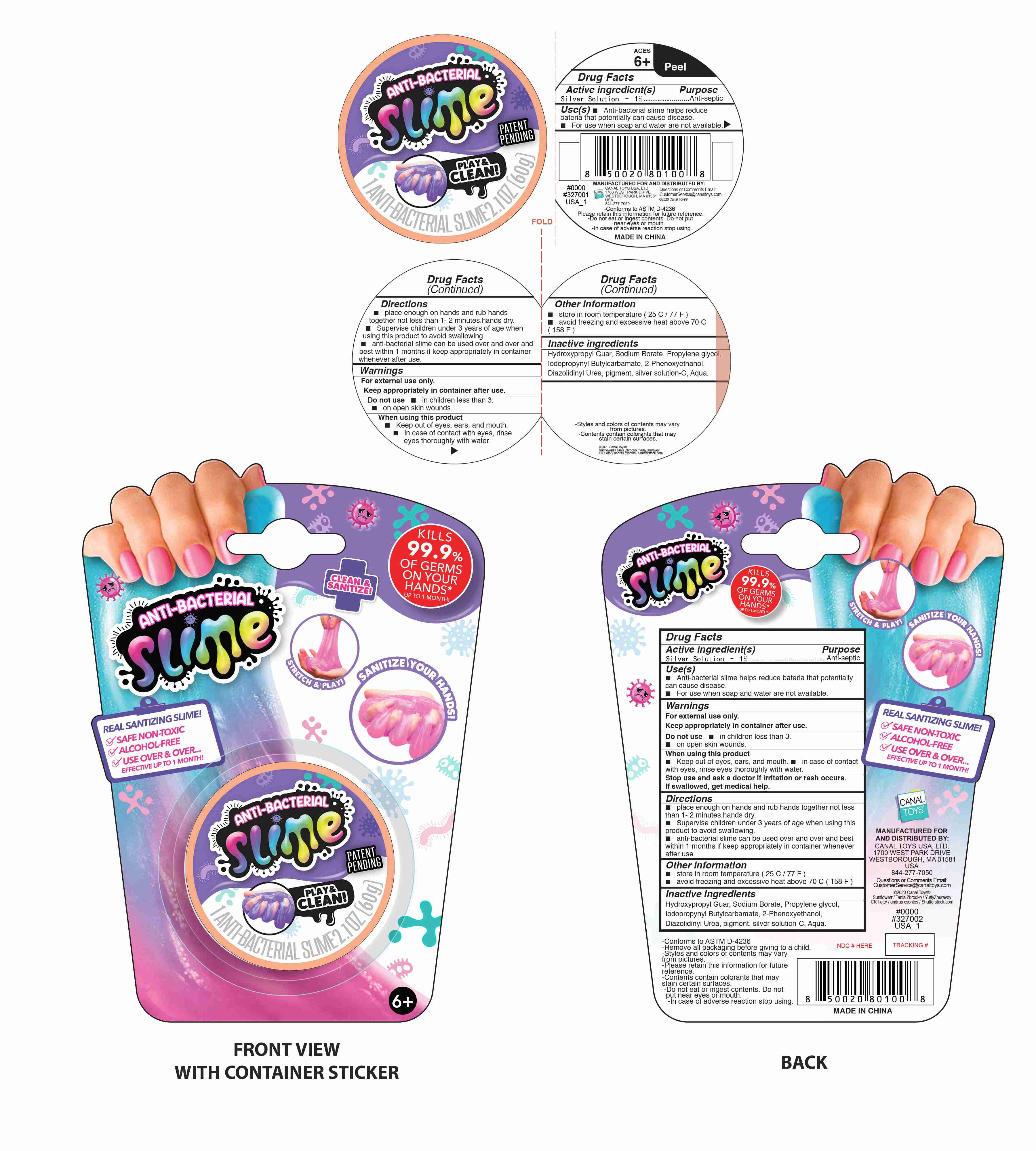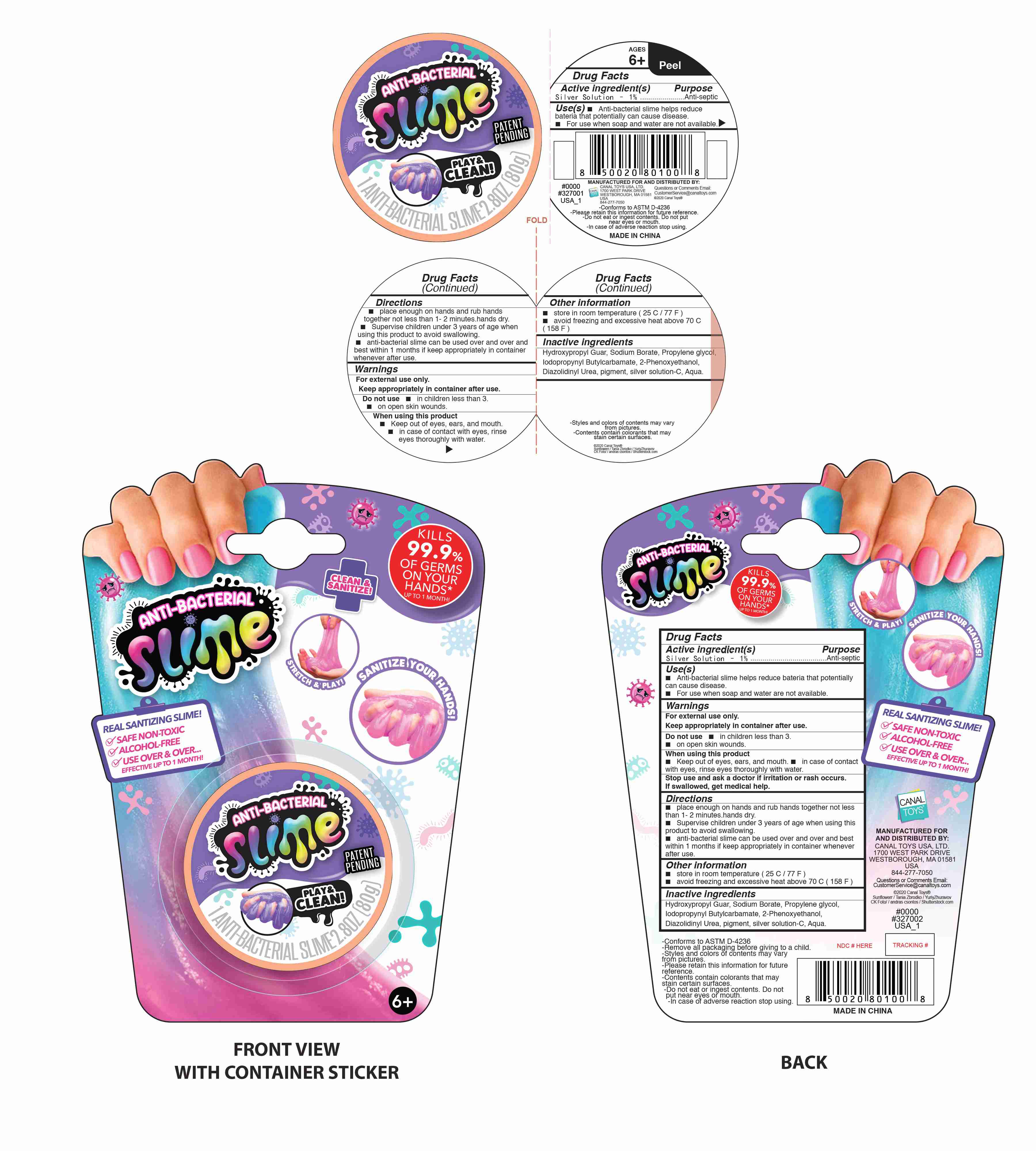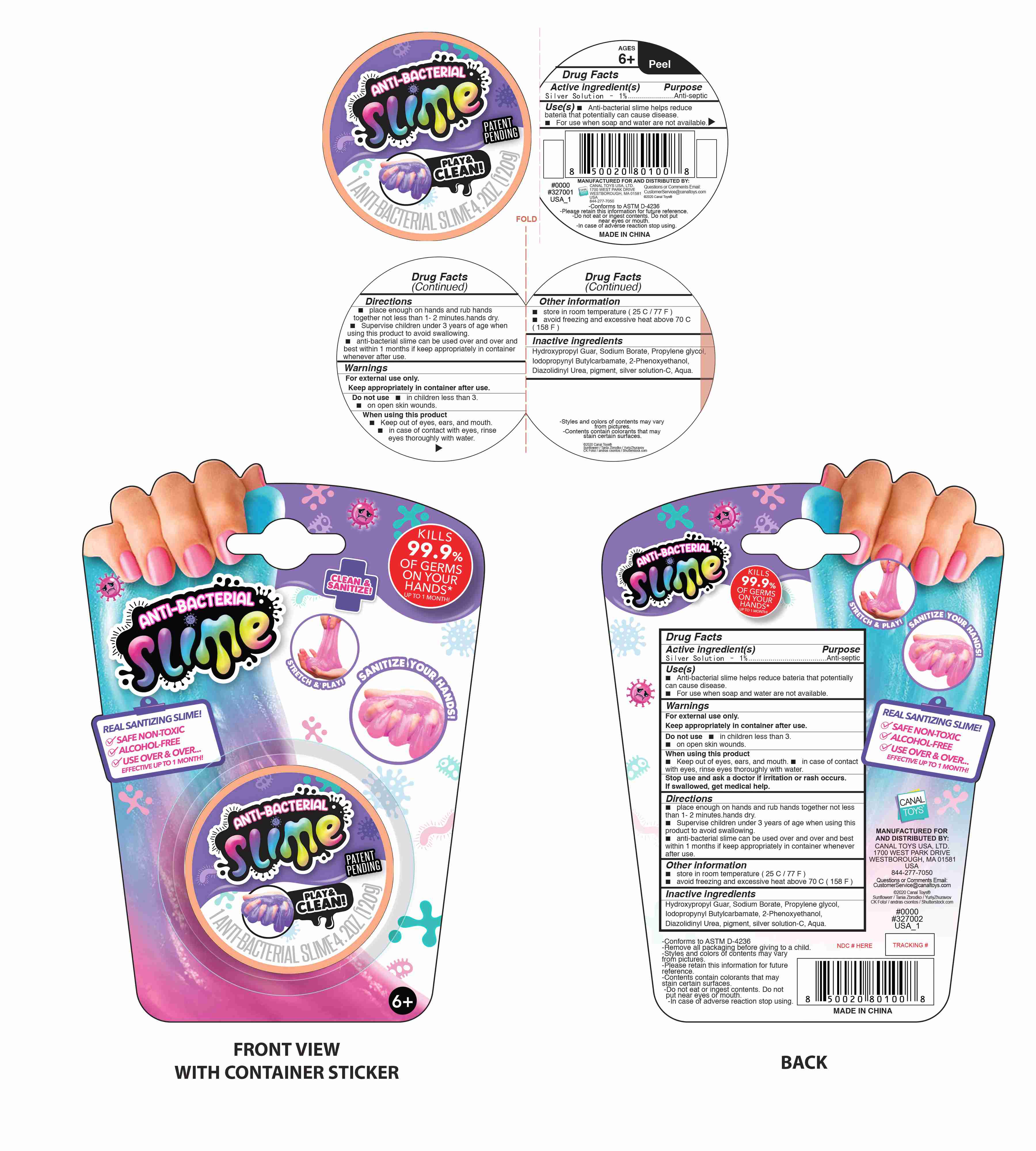 DRUG LABEL: ANTI-BACTERIAL SLIME
NDC: 78048-013 | Form: GEL
Manufacturer: Dongguan City Dexu Toys Co., Ltd.
Category: otc | Type: HUMAN OTC DRUG LABEL
Date: 20200829

ACTIVE INGREDIENTS: SILVER CATION 1 g/100 g
INACTIVE INGREDIENTS: DIAZOLIDINYL UREA; GUARAPROLOSE (3500 MPA.S AT 1%); WATER; SODIUM BORATE; PROPYLENE GLYCOL; BENZALKONIUM CHLORIDE; PHENOXYETHANOL; IODOPROPYNYL BUTYLCARBAMATE

78048-013
ANTI-BACTERIAL SLIME

Active Ingredient(s)

Silver Solution- 1%

Purpose

Anti-septic

Use

Anti-bacterial slime helps reduce bateria that potentially can cause disease.
For use when soap and water are not available.

Warnings

For external use only.
Keep appropriately in container after use.

Do not use

in children less than 3.
on open skin wounds.

WHEN USING

Keep out of eyes, ears, and mouth.
in case of contact with eyes, rinse eyes thoroughly with water.

Stop use and ask a doctor if irritation or rash occurs.
If swallowed, get medical help.

Directions

place enough on hands and rub hands together not less than 1- 2 minutes.hands dry.
Supervise children under 3 years of age when using this product to avoid swallowing.
anti-bacterial slime can be used over and over and best within 1 months if keep appropriately in container whenever after use.

Other information

store in room temperature (25 C/77 F)
avoid freezing and excessive heat above 70 C (158 F)

Inactive ingredients

Hydroxypropyl Guar, Sodium Borate, Propylene glycol,
lodopropynyl Butylcarbamate, 2-Phenoxyethanol,
Diazolidinyl Urea, pigment, silver solution-C, Aqua.